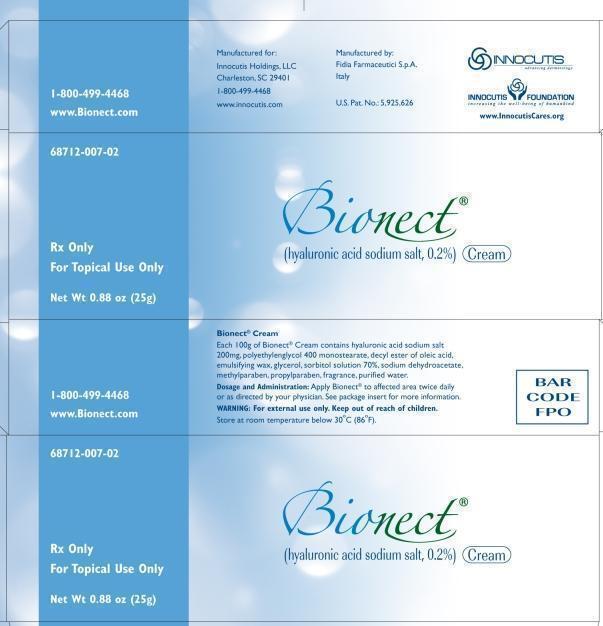 DRUG LABEL: Bionect
NDC: 68712-007
Manufacturer: Innocutis Holdings LLC
Category: other | Type: PRESCRIPTION MEDICAL DEVICE LABEL
Date: 20120921
INACTIVE INGREDIENTS: HYALURONIC ACID .2 g/1 g; PEG-8 STEARATE; DECYL OLEATE; WHITE WAX; GLYCERYL MONOSTEARATE; SORBITOL; SODIUM DEHYDROACETATE; METHYLPARABEN; PROPYLPARABEN; WATER

Bionect Cream (Hyaluronic Acid Sodium Salt 0.2%)

Description

Bionect Cream is a white Viscous cream. The principal componet is the sodium salt of hyaluronic acid (0.02%). Hyaluronic acid is a biological polysaccharide (glycisaminiglycan) and is a major componet of the estracellular matrix of the connective tissues.

Indications

Bionect is indicated for the dressing and management of partial to full thickness dermal ulcers (pressure sores, venous stasis ulcers, arterial ulcers, diabetic ulcers), wounds including cuts, abrasions, donor sites, and post operatice incisions, irritations of the skin, and first and second degree burns, The dressing is intended to cover a wound or burn on a patient's skin, and protect against abrasion, friction and desiccation.

Directions

The wounds or ulcers should be cleaned and disinfected prior to treatment. In the event of the long-standing ulcers, it may be advisable to clean and/or to debride the wound by surgical or enzymatic means, prior to treatment. Apply a thin layer of Bionect without extensive rubbing onto the wound surface, two or three times per day. Cover the lesion area with a sterile gauze pad and, if necessary, with an elastic or compressive bandage.

Warning

If conditions worsens, consult your physician immediately. Keep this product out of the reach of children. The prolonged use of the product may give rise to sensitization phenomena. Should this happen, discontinue the treatment and follow a suitable therapy. Do not use the product after expiration date reported on the package.

Ingredients

Hyaluronic acid sodium salt (Hyalastine), polyethyleneglycol 400 monostearate, decyl ester of oleic, emulsifying wax, glycerol, sorbitol solution 70%, sodium dehydroacetate, methylparaben, propylparaben, fragrance, purified water.

Contraindication

Do not administer to patients with known hypersensitivity to this product.

Drug Interactions

Do not use concomitantly with disinfectants containing quaternary ammonium salts because hyaluronic acid can precipitate in their presence. The concomitant topical treatment of wounds with antibiotics or other local agents has never given rise to interactions or incompatibilities with Bionect.

Precautions

Each tube of Bionect should be used by one patient only in order to reduce the risk of cross infection.

Adverse Reactions

All suspected adverse reactions occurring during the treatment with Bionect should be reported to your doctor.

How Supplied

Bionect Cream is supplied in a:
25g cream Tube - NHRIC 68712-0007-02
50g Cream Tube - NHRIC 68712-0007-03
60g Cream Tube - NHRIC 68712-0007-04
Manufactured for: Inncoutis Holdings LLC, Charleston SC 29401
1-800-499-4468 www.Innocutis.com, www.Bionect.com
Manufactured by: Fidia Farmacutici S.p.A, Italy
U.S. Pat. No.: 5,925,626

Storage

Please store Bionect at room temperature. Bionect Cream may be stored for up to 24 months.